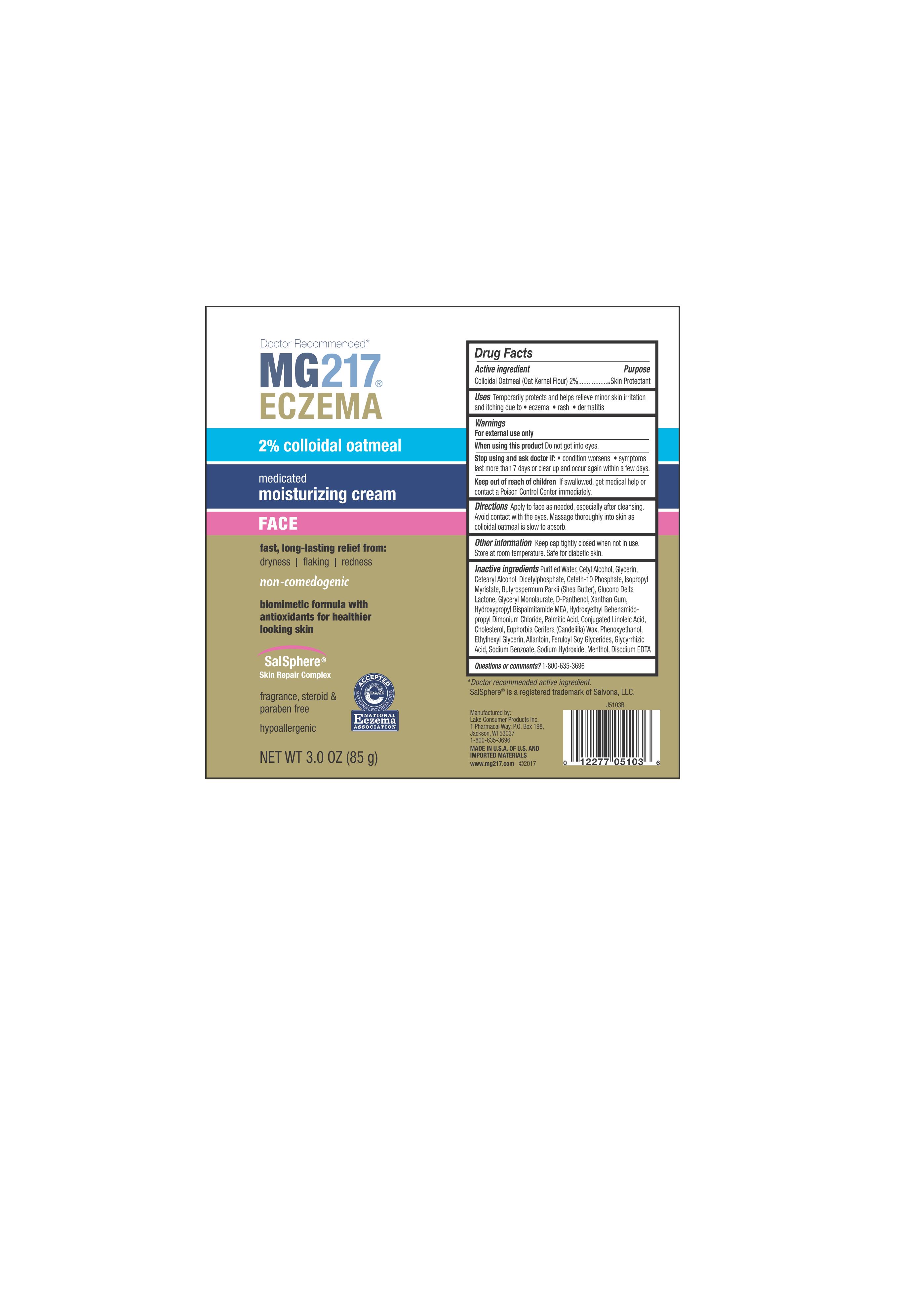 DRUG LABEL: MG217 Eczema Face
NDC: 68093-7245 | Form: LOTION
Manufacturer: Wisconsin Pharmacal Company
Category: otc | Type: HUMAN OTC DRUG LABEL
Date: 20171130

ACTIVE INGREDIENTS: OATMEAL 0.02 g/1 g
INACTIVE INGREDIENTS: ISOSTEARYL FERULATE; WATER; GLYCERIN; ETHYLHEXYLGLYCERIN; EDETATE DISODIUM; DIHEXADECYL PHOSPHATE; CETETH-10 PHOSPHATE; ISOPROPYL MYRISTATE; DEXPANTHENOL; PHENOXYETHANOL; GLUCONOLACTONE; GLYCERYL 1-LAURATE; XANTHAN GUM; HYDROXYPROPYL BISPALMITAMIDE MONOETHANOLAMIDE; HYDROXYETHYL BEHENAMIDOPROPYL DIMONIUM CHLORIDE; PALMITIC ACID; CHOLESTEROL; CETYL ALCOHOL; CONJUGATED LINOLEIC ACID; CANDELILLA WAX; ALLANTOIN; GLYCYRRHIZIN; SODIUM BENZOATE; SODIUM HYDROXIDE; MENTHOL, (+)-; CETOSTEARYL ALCOHOL; SHEA BUTTER

Active Ingredient

Colloidal Oatmeal (Oat Kernel Flour) 2%

Purpose

Skin Protectant

Uses

Temporarily protects and helps relieve minor skin irritation and itching due to

- eczema
- rash
- dermatitis

WARNINGS

For external use only

When using this product Do not get into eyes

Stop using and ask doctor if:

• condition worsens

• symptoms last more than 7 days or clear up and occur again within a few days.

Keep out of reach of children

If swallowed, get medical help or contact a Poison Control Center immediately

Directions

Apply as needed, especially after bathing. Massage thoroughly into skin as colloidal oatmeal is slow to absorb.

Other Information

Keep cap tightly closed when not in use. Store at room temperature. Safe for diabetic skin

Inactive ingredients

Puriﬁed Water, Cetyl Alcohol, Glycerin, Cetearyl Alcohol, Dicetylphosphate, Ceteth-10 Phosphate, Isopropyl Myristate, Butyrospermum Parkii (Shea Butter), Glucono Delta Lactone, Glyceryl Monolaurate, D-Panthenol, Xanthan Gum, Hydroxypropyl Bispalmitamide MEA, Hydroxyethyl Behenamido-propyl Dimonium Chloride, Palmitic Acid, Conjugated Linoleic Acid, Cholesterol, Euphorbia Cerifera (Candelilla) Wax, Phenoxyethanol, Ethylhexyl Glycerin, Allantoin, Feruloyl Soy Glycerides, Glycyrrhizic Acid, Sodium Benzoate, Sodium Hydroxide, Menthol, Disodium EDTA

Questions or comments?

1-800-635-3696